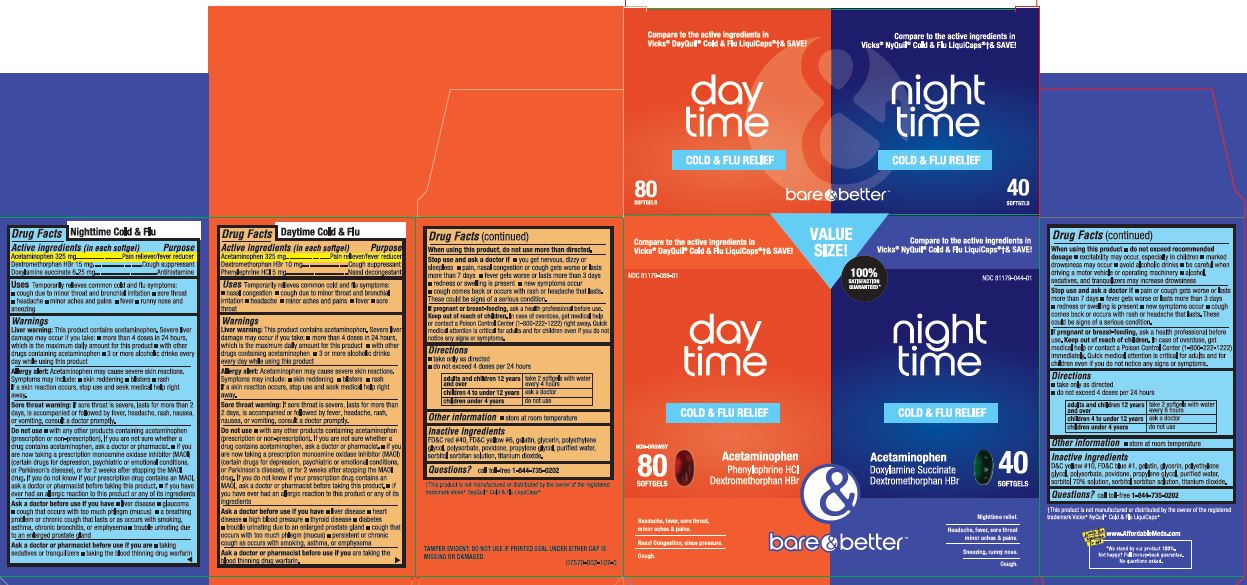 DRUG LABEL: DayTime NightTime Cold and Flu Relief
NDC: 81179-803 | Form: KIT | Route: ORAL
Manufacturer: YET HEALTH GROUP LLC
Category: otc | Type: HUMAN OTC DRUG LABEL
Date: 20240103

ACTIVE INGREDIENTS: DEXTROMETHORPHAN HYDROBROMIDE 15 mg/1 1; DOXYLAMINE SUCCINATE 6.25 mg/1 1; ACETAMINOPHEN 325 mg/1 1; ACETAMINOPHEN 325 mg/1 1; DEXTROMETHORPHAN HYDROBROMIDE 10 mg/1 1; PHENYLEPHRINE HYDROCHLORIDE 5 mg/1 1
INACTIVE INGREDIENTS: WATER; PROPYLENE GLYCOL; POVIDONE; FD&C BLUE NO. 1; GELATIN; GLYCERIN; SORBITOL; POLYETHYLENE GLYCOL 1000000; POLYSORBATE 80; TITANIUM DIOXIDE; D&C YELLOW NO. 10; SORBITAN; SORBITOL; WATER; PROPYLENE GLYCOL; FD&C RED NO. 40; POLYETHYLENE GLYCOL, UNSPECIFIED; FD&C YELLOW NO. 6; POVIDONE, UNSPECIFIED; GELATIN; GLYCERIN; POLYSORBATE 80; TITANIUM DIOXIDE; SORBITAN

YET (as PLD) - BARE & BETTER DAYTIME/NIGHTTIME COLD & FLU RELIEF (81179-803)

NIGHTTIME COLD & FLU Active ingredients (in each softgel)

Acetaminophen 325 mg

Dextromethorphan HBr 15 mg

Doxylamine succinate 6.25 mg

DAYTIME COLD & FLU Active ingredients (in each softgel)

Acetaminophen 325 mg

Dextromethorphan HBr 10 mg

Phenylephrine HCl 5 mg

NIGHTTIME COLD & FLU Purpose

Pain reliever/fever reducer

Cough suppressant

Antihistamine

DAYTIME COLD & FLU Purpose

Pain reliever/fever reducer

Cough suppressant

Nasal decongestant

NIGHTTIME COLD & FLU Uses

temporarily relieves common cold/flu symptoms:

- cough due to minor throat and bronchial irritation
- sore throat
- headache
- minor aches and pains
- fever
- runny nose and sneezing

DAYTIME COLD & FLU Uses

Temporarily relieves common cold/flu symptoms:

- nasal congestion
- cough due to minor throat and bronchial irritation
- headache
- minor aches and pains
- fever
- sore throat

Warnings

Liver warning: This product contains acetaminophen. Severe liver damage may occur if you take

- more than 4 doses in 24 hours, which is the maximum daily amount for this product
- with other drugs containing acetaminophen
- 3 or more alcoholic drinks every day while using this product

Allergy alert: Acetaminophen may cause severe skin reactions. Symptoms may include:

- skin reddening
- blisters
- rash

If a skin reaction occurs, stop use and seek medical help right away.

Sore throat warning: If sore throat is severe, persists for more than 2 days, is accompanied or followed by fever, headache, rash, nausea, or vomiting, consult a doctor promptly.

Do not use

- with any other drug containing acetaminophen (prescription or nonprescription). If you are not sure whether a drug contains acetaminophen, ask a doctor or pharmacist.
- if you are now taking a prescription monoamine oxidase inhibitor (MAOI) (certain drugs for depression, psychiatric, or emotional conditions, or Parkinson’s disease), or for 2 weeks after stopping the MAOI drug. If you do not know if your prescription drug contains an MAOI, ask a doctor or pharmacist before taking this product.
- if you have ever had an allergic reaction to this product or any of its ingredients

NIGHTTIME COLD & FLU Ask a doctor before use if you have

- liver disease
- glaucoma
- cough that occurs with too much phlegm (mucus)
- a breathing problem or chronic cough that lasts or as occurs with smoking, asthma, chronic bronchitis, or emphasema
- trouble urinating due to an enlarged prostate gland

DAYTIME COLD & FLU Ask a doctor before use if you have

- liver disease
- heart disease
- high blood pressure
- thyroid disease
- diabetes
- trouble urinating due to an enlarged prostate gland
- cough that occurs with too much phlegm (mucus)
- persistent or chronic cough such as occurs with smoking, asthma, chronic bronchitis, or emphysema

NIGHTTIME COLD & FLU Ask a doctor or pharmacist before use if you are

- taking sedatives or tranquilizers
- taking the blood thinning drug warfarin

DAYTIME COLD & FLU Ask a doctor or pharmacist before use if you are

taking the blood thinning drug warfarin

NIGHTTIME COLD & FLU When using this product

- do not exceed recommended dosage
- excitability may occur, especially in children
- marked drowsiness may occur
- avoid alcoholic drinks
- be careful when driving a motor vehicle or operating machinery
- alcohol, sedatives, and tranquilizers may increase drowsiness

DAYTIME COLD & FLU When using this product

do not use more than directed.

NIGHTTIME COLD & FLU Stop use and ask a doctor if

- pain or cough gets worse or lasts more than 7 days
- fever gets worse or lasts more than 3 days
- redness or swelling is present
- new symptoms occur
- cough comes back or occurs with rash or headache that lasts.

These could be signs of a serious condition.

DAYTIME COLD & FLU Stop use and ask a doctor if

- you get nervous, dizzy or sleepless
- pain, nasal congestion, or cough gets worse or lasts more than 7 days
- fever gets worse or lasts more than 3 days
- redness or swelling is present
- new symptoms occur
- cough comes back or occurs with rash or headache that lasts.

These could be signs of a serious condition.

If pregnant or breast-feeding,

ask a health professional before use.

Keep out of reach of children.

In case of overdose, get medical help or contact a Poison Control Center (1-800-222-1222) right away. Quick medical attention is critical for adults as well as for children even if you do not notice any signs or symptoms.

NIGHTTIME COLD & FLU Directions

- take only as directed
- do not exceed 4 doses per 24 hrs

adults & children 12 yrs & over | 2 softgels with water every 6 hrs
children 4 to under 12 yrs | ask a doctor
children under 4 yrs | do not use

DAYTIME COLD & FLU Directions

take only as directed
do not exceed 4 doses per 24 hrs

adults & children 12 yrs & over | 2 softgels with water every 4 hrs
children 4 to under 12 yrs | ask a doctor
children under 4 yrs | do not use

Other information

- store at room temperature

NIGHTTIME COLD & FLU Inactive ingredients

D&C YELLOW #10, FD&C BLUE #1, GELATIN, GLYCERIN, POLYETHYLENE GLYCOL, POLYSORBATE, POVIDONE, PROPYLENE GLYCOL, PURIFIED WATER, SORBITOL 70% SOLUTION, SORBITOL SORBITAN SOLUTION, TITANIUM DIOXIDE.

DAYTIME COLD & FLU Inactive ingredients

FD&C RED #40, FD&C YELLOW #6, GELATIN, GLYCERIN, POLYETHYLENE GLYCOL, POLYSORBATE, POVIDONE, PROPYLENE GLYCOL, PURIFIED WATER, SORBITOL SORBITAN SOLUTION, TITANIUM DIOXIDE.

Questions or comments?

CALL TOLL-FREE 1-844-735-0202